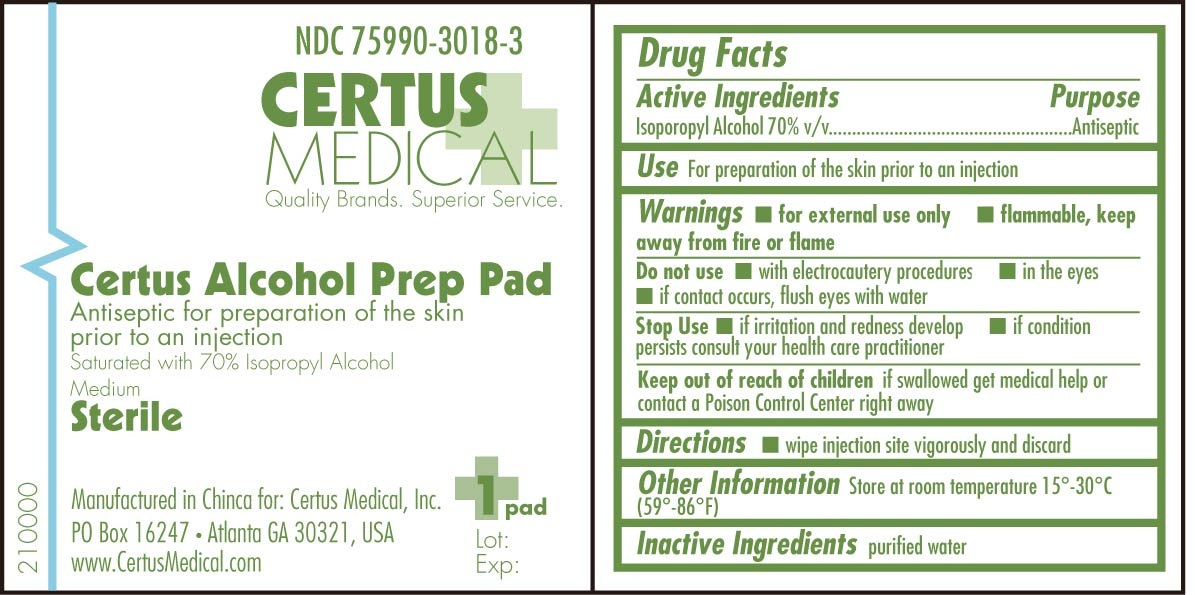 DRUG LABEL: Certus Alcohol Prep
NDC: 75990-3018 | Form: SWAB
Manufacturer: Certus Medical, Inc.
Category: otc | Type: HUMAN OTC DRUG LABEL
Date: 20181126

ACTIVE INGREDIENTS: ISOPROPYL ALCOHOL 0.7 mL/1 mL
INACTIVE INGREDIENTS: WATER

Certus Alcohol Prep Pad 210000 Drug Facts and Label

Drug Facts Box OTC-Active Ingredient Section

Isopropyl Alcohol 70% v/v

Drug Facts Box OTC-Purpose Section

Antiseptic

Drug Facts Box OTC-Indications and Usage Section

For preparation of the skin prior to an injection

Drug Facts Box OTC-Warnings Section

for external use only

flammable, keep away from fire or flame

Drug Facts Box OTC-Do Not Use Section

with electrocautery procedures

in the eyes

if contact occurs , flush eyes with water

Drug Facts Box OTC-Stop Use Section

if irritation and redness develop

if condition persists consult your health care practitioner

Drug Facts Box OTC-Keep Out Of Reach Of Children Section

if swallowed get medical help or call a Poison Control Center right away

Drug Facts Box OTC-Dosage & Administration Section

wipe injection site vigorously and discard

Drug Facts Box OTC-General Precautions Section

Store at room temperature 15 degrees - 30 degrees C (59 degrees - 86 degrees F)

Drug Facts Box OTC-Inactive Ingredient Section

purified water

Certus Alcohol Prep Pad 210000 pouch

Certus Alcohol Prep Pad